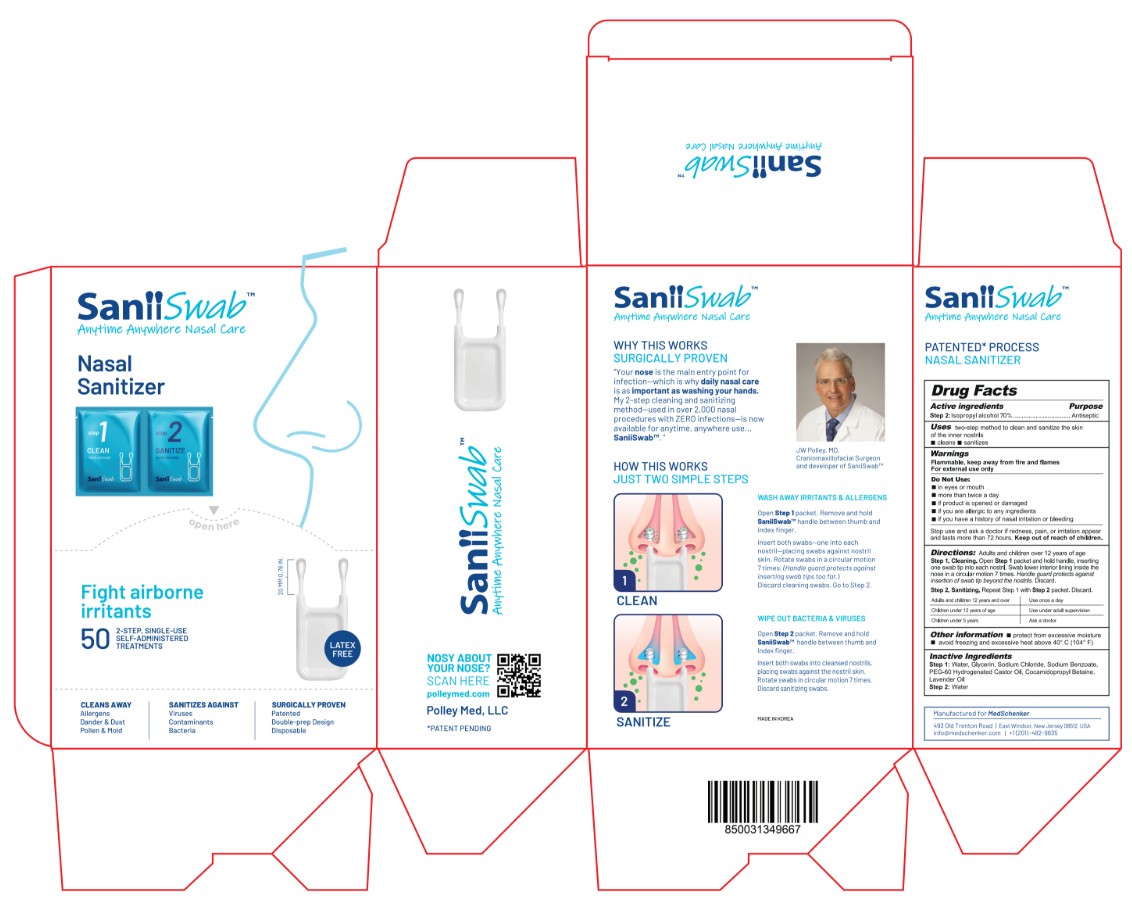 DRUG LABEL: Saniiswab
NDC: 84456-026 | Form: SWAB
Manufacturer: POLLEY MED LLC
Category: otc | Type: HUMAN OTC DRUG LABEL
Date: 20250320

ACTIVE INGREDIENTS: ISOPROPYL ALCOHOL 0.7 g/1 g
INACTIVE INGREDIENTS: PEG-60 HYDROGENATED CASTOR OIL; SODIUM CHLORIDE; GLYCERIN; SODIUM BENZOATE; COCAMIDOPROPYL BETAINE; WATER; LAVENDER OIL

ACTIVE INGREDIENT

Isopropyl alcohol 70%. Purpose: Antiseptic

PURPOSE

Antiseptic

INDICATIONS AND USAGE

Two-step method to clean and sanitize the skin of the lower inner nostrils
■ cleans ■ sanitizes

WARNINGS

Flammable, keep away from fire and flames
For external use only

Do Not Use:

- In eyes or mouth
- More than twice a day
- If product is opened or damaged
- If you are allergic to any ingredients
- If you have a history of nasal irritation or bleeding

Stop use and ask a doctor if redness, pain, or irritation appear and lasts more than 24 hours. Keep out of reach of children.

DOSAGE AND ADMINISTRATION

Adults and children over 12 years of age
Step 1. Cleaning. Open Step 1 packet and hold handle, inserting one swab tip into each nostril. Swab lower interior skin inside the nose in a circular motion 7 times. Handle guard protects against insertion of swab tip beyond the nostrils. Discard.
Step 2. Sanitizing. Repeat Step 1 with Step 2 packet. Discard.

- Adults and children 12 years and over- Use once a day
- Children under 12 years of age- Use under adult supervision
- Children under 5 years- Ask a doctor

STORAGE AND HANDLING

Protect from excessive moisture
Avoid freezing and excessive heat above 40 °C (104 °F)

INACTIVE INGREDIENT

water, glycerin, sodium chloride, sodium benzoate, PEG-60 hydrogenated castor oil, cocamidopropyl betaine, lavender oil

Keep out of reach of children.